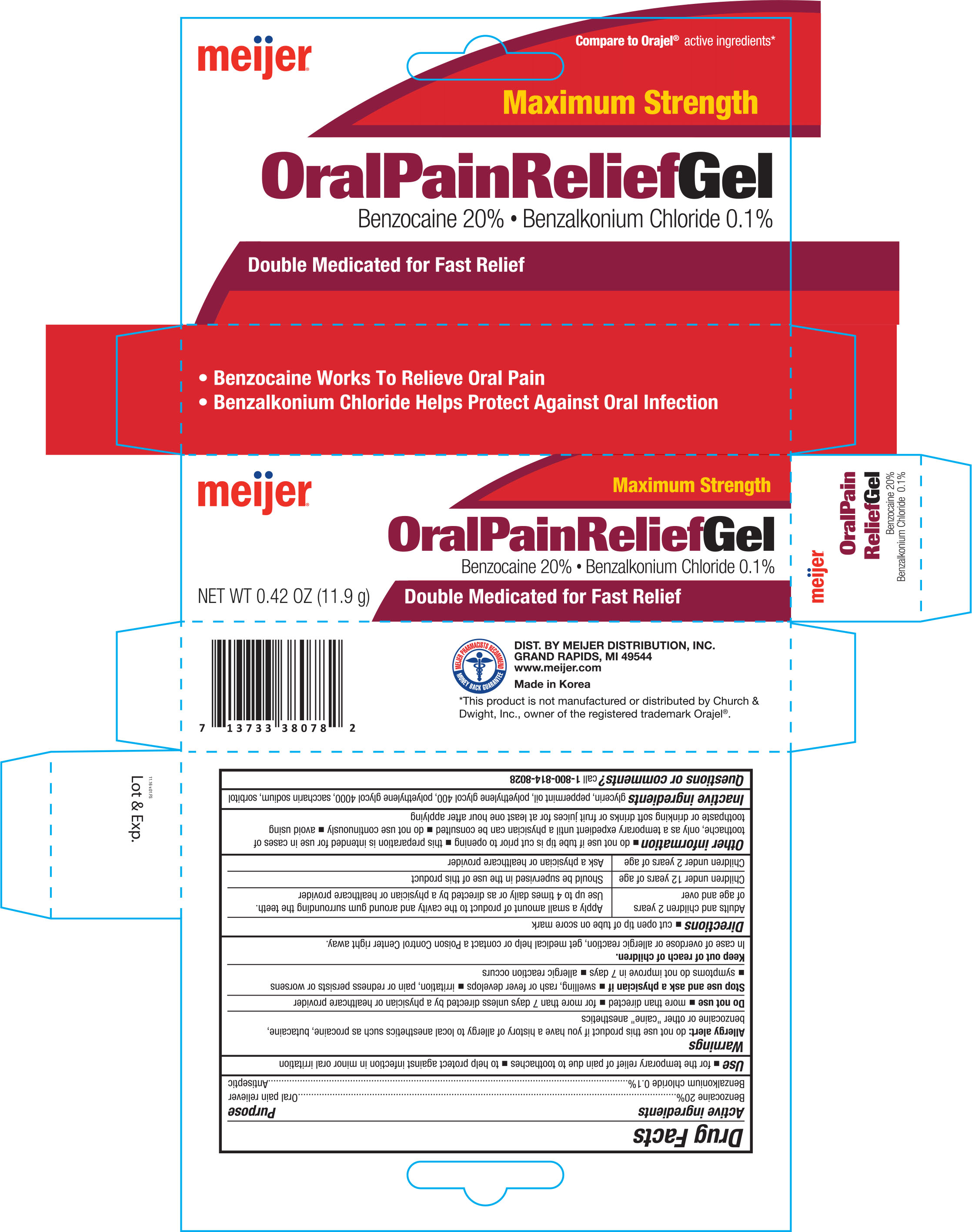 DRUG LABEL: Meijer Maximum Strength Oral Pain Relief
NDC: 41250-782 | Form: GEL
Manufacturer: MEIJER DISTRIBUTION INC
Category: otc | Type: HUMAN OTC DRUG LABEL
Date: 20161208

ACTIVE INGREDIENTS: BENZOCAINE 200 mg/1 g; BENZALKONIUM CHLORIDE 1 mg/1 g
INACTIVE INGREDIENTS: GLYCERIN; PEPPERMINT OIL; POLYETHYLENE GLYCOL 400; POLYETHYLENE GLYCOL 4000; SACCHARIN SODIUM; SORBITOL

Active ingredients Purpose

Benzocaine 20%..............................Oral pain reliever

Benzalkonium chloride 0.1%............Antiseptic

Use

- for the temporary relief of pain due to toothaches
- to help protect against infection in minor oral irritation

Warnings

Allergy alert: do not use this product if you have a history of allergy to local anesthetics such as procaine, butacaine, benzocaine or other "caine" anesthetics

Do not use

- more than directed
- for more than 7 days unless directed by a physician or healthcare provider

Stop use and ask a physician if

- swelling, rash or fever develops
- irritation, pain or redness persists or worsens
- symptoms do not improve in 7 days
- allergic reaction occurs

Keep out of reach of children.

In case of overdose or allergic reaction, get medical help or contact a Poison Control Center right away.

Directions

- cut open tip of tube on score mark
  Adults and children 2 years of age and over | Apply a small amount of product to the cavity around gum surrounding the teeth.
  Children under 12 years of age | Should be supervised in the use of this product
  Children under 2 years of age | Ask a physician or healthcare provider

Other information

- do not use if tube tip is cut prior to opening
- this preparation is intended for use in cases of toothache, only as a temporary expedient until a physician can be consulted
- do not use continuously
- avoid using toothpaste or drinking soft drinks or fruit juices for at least one hour after applying

INACTIVE INGREDIENT

Inactive ingredients glycerin, peppermint oil, polyethylene glycol 400, polyethylene glycol 4000, saccharin sodium, sorbitol

DOSAGE AND ADMINISTRATION

DIST. BY MEIJER DISTRIBUTION, INC.

GRAND RAPIDS, MI 49544

www.meijer.com

Made in Korea